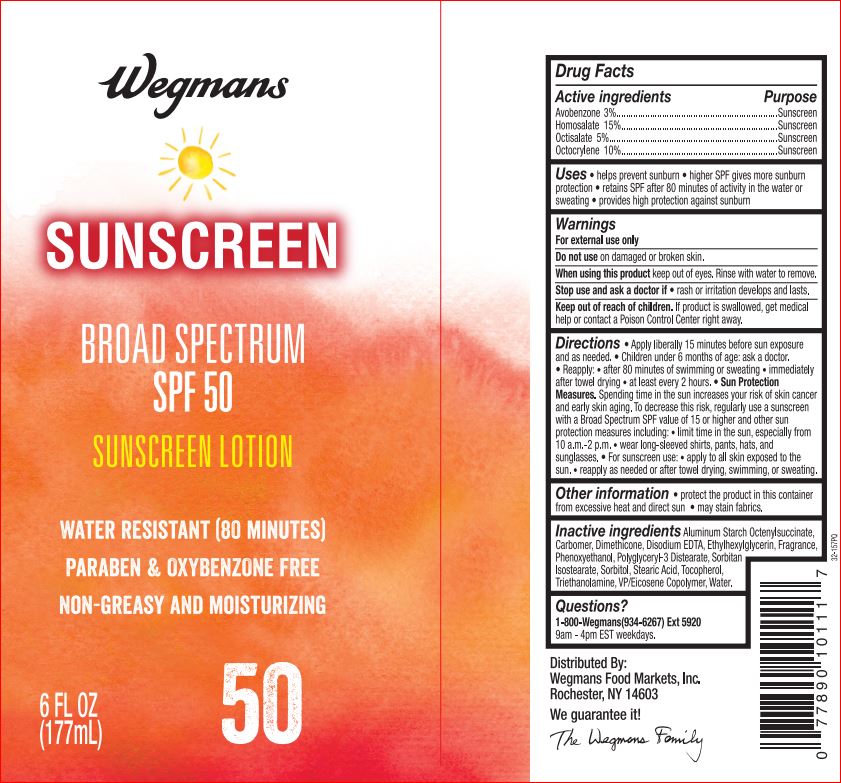 DRUG LABEL: Sunscreen SPF 50
NDC: 47124-113 | Form: LOTION
Manufacturer: Wegman
Category: otc | Type: HUMAN OTC DRUG LABEL
Date: 20180511

ACTIVE INGREDIENTS: Avobenzone 3 g/100 mL; Homosalate 15 g/100 mL; Octisalate 5 g/100 mL; Octocrylene 10 g/100 mL
INACTIVE INGREDIENTS: Aluminum Starch Octenylsuccinate; CARBOMER HOMOPOLYMER TYPE C (ALLYL PENTAERYTHRITOL CROSSLINKED); Dimethicone; EDETATE DISODIUM ANHYDROUS; Ethylhexylglycerin; Phenoxyethanol; Polyglyceryl-3 Distearate; Sorbitan Isostearate; Sorbitol; Stearic Acid; Tocopherol; EICOSYL POVIDONE; TROLAMINE; Water

Drug Facts

Active ingredients Purpose
Avobenzone 3%...................................................................Sunscreen
Homosalate 15%.................................................................Sunscreen
Octisalate 5%......................................................................Sunscreen
Octocrylene 10%.................................................................Sunscreen

INDICATIONS AND USAGE

Uses • helps prevent sunburn • higher SPF gives more sunburn
protection • retains SPF after 80 minutes of activity in the water or
sweating • provides high protection against sunburn

Warnings
For external use only
Do not use on damaged or broken skin.
When using this product keep out of eyes. Rinse with water to remove.
Stop use and ask a doctor if • rash or irritation develops and lasts

Keep out of reach of children. If product is swallowed, get medical help or contact a Poison Control Center right away

DOSAGE AND ADMINISTRATION

Directions • Apply liberally 15 minutes before sun exposure
and as needed. • Children under 6 months of age: ask a doctor.
• Reapply: • after 80 minutes of swimming or sweating • immediately
after towel drying • at least every 2 hours. • Sun Protection
Measures. Spending time in the sun increases your risk of skin cancer
and early skin aging. To decrease this risk, regularly use a sunscreen
with a Broad Spectrum SPF value of 15 or higher and other sun
protection measures including: • limit time in the sun, especially from
10 a.m.-2 p.m. • wear long-sleeved shirts, pants, hats, and
sunglasses. • For sunscreen use: • apply to all skin exposed to the
sun. • reapply as needed or after towel drying, swimming, or sweating

Other information • protect the product in this container from excessive heat and direct sun • may stain fabrics

Inactive ingredients

Aluminum Starch Octenylsuccinate,
Carbomer, Dimethicone, Disodium EDTA, Ethylhexylglycerin, Fragrance,
Phenoxyethanol, Polyglyceryl-3 Distearate, Sorbitan
Isostearate, Sorbitol, Stearic Acid, Tocopherol,
Triethanolamine, VP/Eicosene Copolymer, Water.

Questions?
1-800-Wegmans(934-6267) Ext 5920
9am - 4pm EST weekdays.